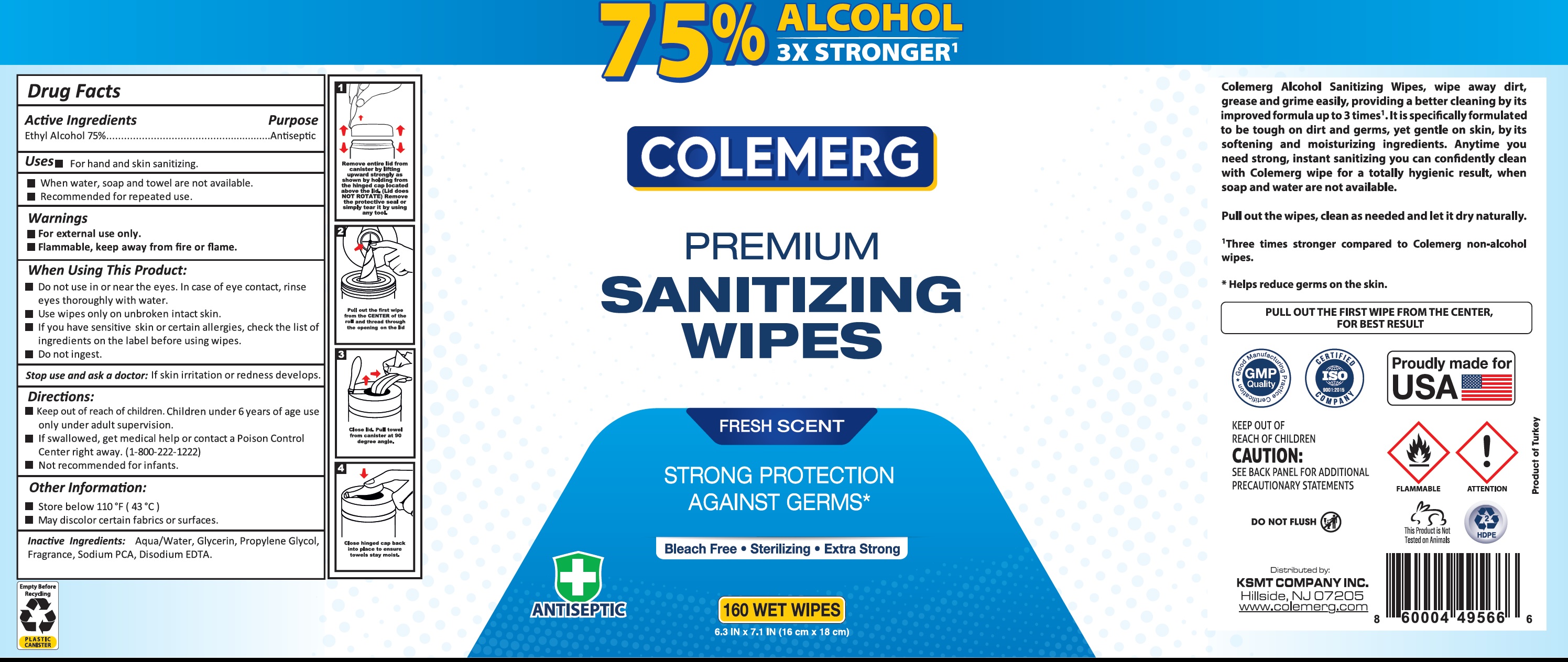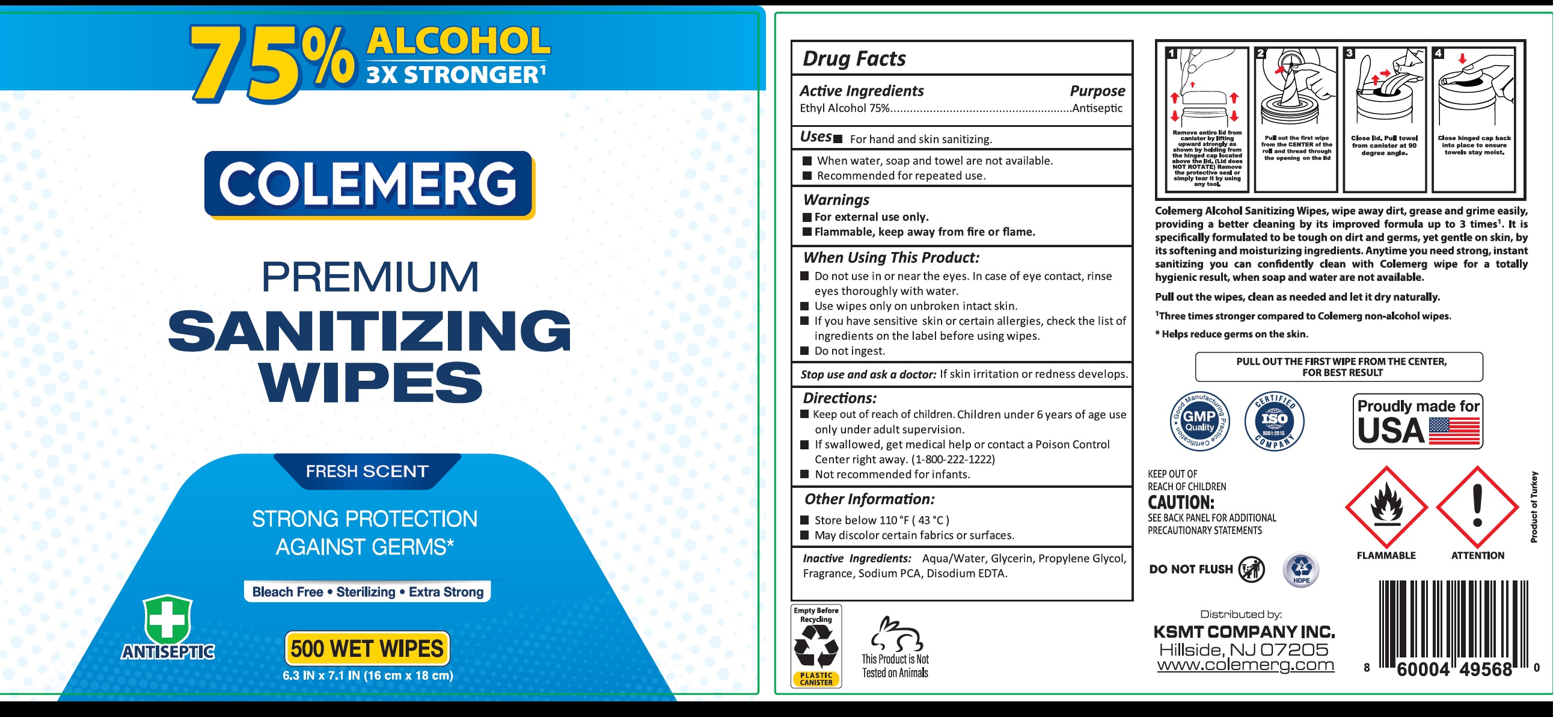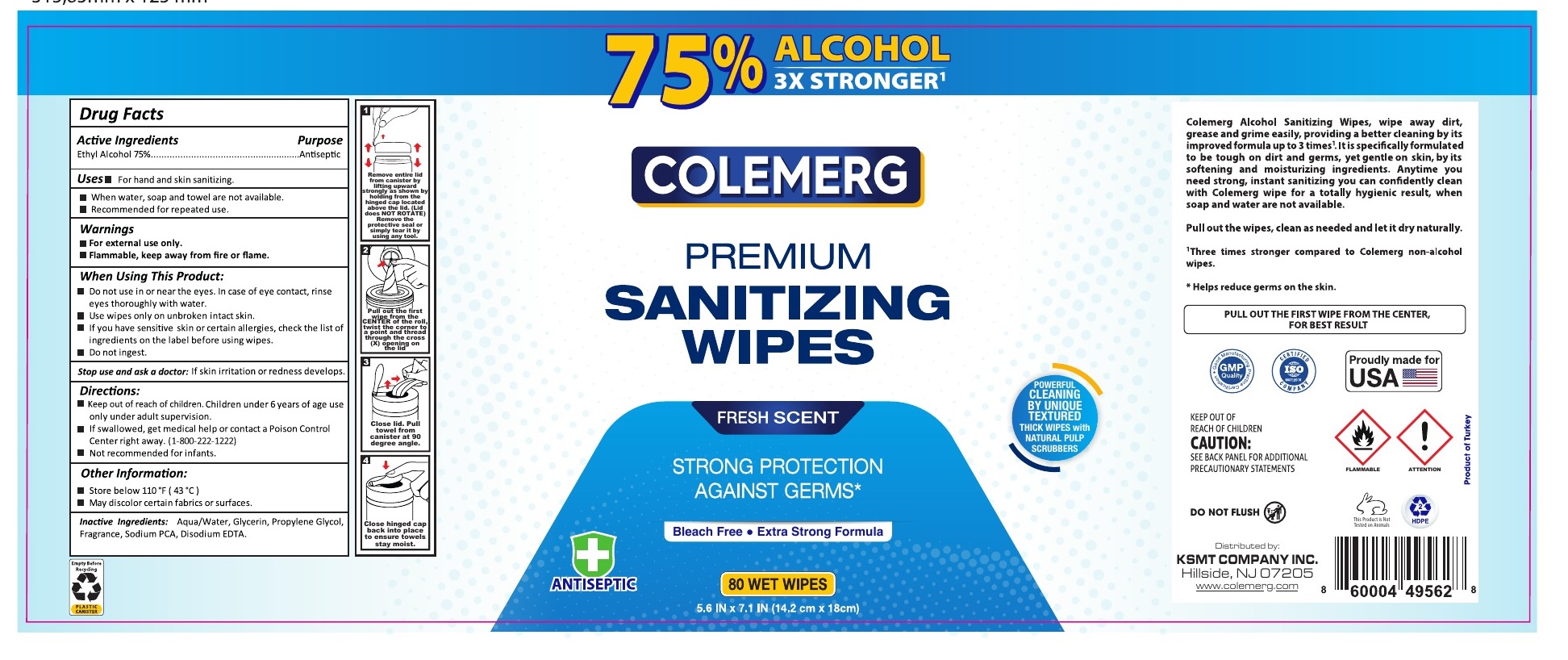 DRUG LABEL: Colemerg Premium Sanitizing Wipes
NDC: 81547-000 | Form: CLOTH
Manufacturer: KSMT COMPANY INCORPORATED
Category: otc | Type: HUMAN OTC DRUG LABEL
Date: 20210219

ACTIVE INGREDIENTS: ALCOHOL 75 mL/100 mL
INACTIVE INGREDIENTS: WATER; GLYCERIN; PROPYLENE GLYCOL; SODIUM PYRROLIDONE CARBOXYLATE; EDETATE DISODIUM ANHYDROUS

Colemerg Premium Sanitizing Wipes, 80 Alcohol wipes

Active Ingredients

Ethyl Alcohol 75%

Purpose

Antiseptic

Uses

- When water, soap and towel are not availble.
- Recommended for repeated use.

Warnings

- For external use only.
- Flammable, keep away from fire or flame.

When Using This Product:

- Do not use in or near the eyes. In case of eye contact, rinse eyes thoroughly with water.
- use wipes only on unbroken intact skin.
- if you have sensitive skin or certain allergies, check the list of ingredients on the label before using wipes.
- Do not ingest.

stop use and ask a doctor:

If skin irritation or redness develops.

Keep out of reach of children.

Children under 6 years of age use only under adult supervision.

Directions:

- If swallowed, get medical help or contact a Poison Control Center right away. (1-800-222-1222)
- Not recommended for infants.

Other Information:

- Store below 110°F (43°C)
- May discolor certain fabrics or surfaces.

Inactive Ingredients:

Aqua/Water, Glycerin, Propylene Glycol, Fragrance, Sodium PCA, Disodium EDTA.